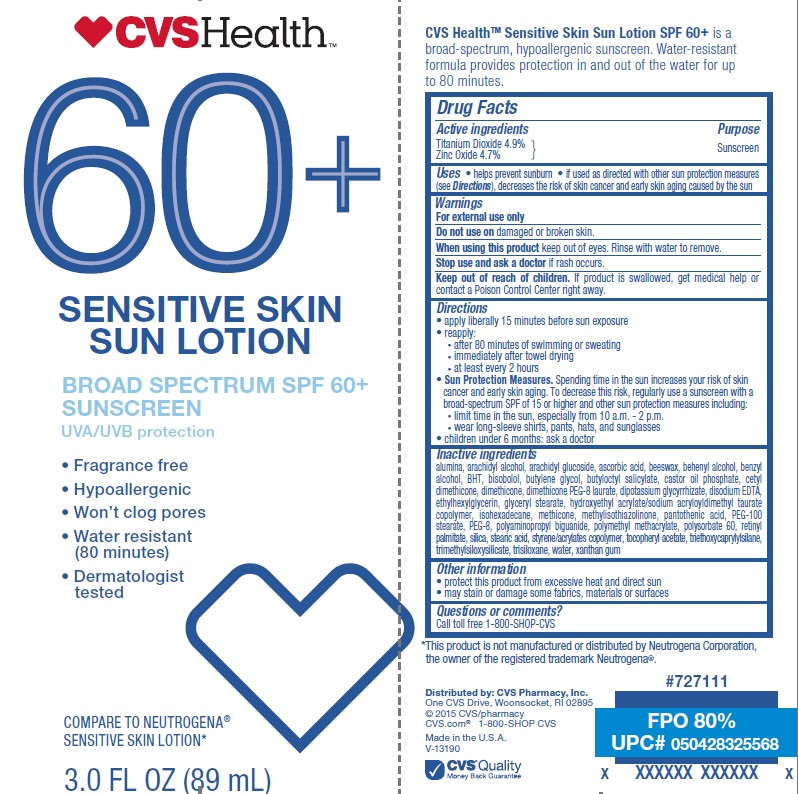 DRUG LABEL: CVS Health
NDC: 69842-123 | Form: LOTION
Manufacturer: CVS Pharmacy
Category: otc | Type: HUMAN OTC DRUG LABEL
Date: 20241022

ACTIVE INGREDIENTS: TITANIUM DIOXIDE 49.39 mg/1 mL; ZINC OXIDE 47.145 mg/1 mL
INACTIVE INGREDIENTS: TRIETHOXYCAPRYLYLSILANE; BUTYLATED HYDROXYTOLUENE; LEVOMENOL; VITAMIN A PALMITATE; METHYLISOTHIAZOLINONE; XANTHAN GUM; CASTOR OIL PHOSPHATE; HYDROXYETHYL ACRYLATE/SODIUM ACRYLOYLDIMETHYL TAURATE COPOLYMER (45000 MPA.S AT 1%); ETHYLHEXYLGLYCERIN; .ALPHA.-TOCOPHEROL ACETATE; EDETATE DISODIUM ANHYDROUS; GLYCYRRHIZINATE DIPOTASSIUM; ASCORBIC ACID; POLYSORBATE 60; POLIHEXANIDE; CALCIUM PANTOTHENATE; CETYL DIMETHICONE 150; WATER; ISOHEXADECANE; BUTYL METHACRYLATE/METHYL METHACRYLATE/METHACRYLIC ACID/STYRENE CROSSPOLYMER; BUTYLOCTYL SALICYLATE; ARACHIDYL ALCOHOL; BUTYLENE GLYCOL; TRISILOXANE; STEARIC ACID; PEG-100 STEARATE; DIMETHICONE PEG-8 LAURATE; GLYCERYL MONOSTEARATE; DOCOSANOL; METHICONE (20 CST); TRIMETHYLSILOXYSILICATE (M/Q 0.6-0.8); BENZYL ALCOHOL; YELLOW WAX; POLYETHYLENE GLYCOL 400; POLY(METHYL METHACRYLATE; 450000 MW); SILICON DIOXIDE; ALUMINUM OXIDE; ARACHIDYL GLUCOSIDE; DIMETHICONE

CVS Health 60+ Sensitive Skin Sun Lotion

Active ingredients

Titanium Dioxide 4.9%, Zinc Oxide 4.7%

Purpose

Sunscreen

Uses

- helps prevent sunburn
- if used as directed with other sun protection measures (see Directions), decreases the risk of skin cancer and early skin aging caused by the sun

Warnings

For external use only

Do not use

on damaged or broken skin

When using this product

keep out of eyes. Rinse with water to remove.

Stop use and ask a doctor

if rash occurs.

Keep out of reach of children.

If product is swallowed, get medical help or contact a Poison Control Center right away.

Directions

• apply liberally 15 minutes before sun exposure
• reapply:
• after 80 minutes of swimming or sweating
• immediately after towel drying
• at least every 2 hours
• Sun Protection Measures. Spending time in the sun increases your risk of skin cancer and early skin aging. To decrease this risk, regularly use a sunscreen with a Broad Spectrum SPF value of 15 or higher and other sun protection measures including:
• limit time in the sun, especially from 10 a.m. - 2 p.m.
• wear long-sleeved shirts, pants, hats, and sunglasses
• children under 6 months: Ask a doctor

Inactive ingredients

alumina, arachidyl alcohol, arachidyl glucoside, ascorbic acid, beeswax, behenyl alcohol, benzyl
alcohol, BHT, bisobolol, butylene glycol, butyloctyl salicylate, castor oil phosphate, cetyl
dimethicone, dimethicone, dimethicone PEG-8 laurate, dipotassium glycyrrhizate, disodium EDTA,
ethylhexylglycerin, glyceryl stearate, hydroxyethyl acrylate/sodium acryloyldimethyl taurate
copolymer, isohexadecane, methicone, methylisothiazolinone, pantothenic acid, PEG-100
stearate, PEG-8, polyaminopropyl biguanide, polymethyl methacrylate, polysorbate 60, retinyl
palmitate, silica, stearic acid, styrene/acrylates copolymer, tocopheryl acetate, triethoxycaprylylsilane,
trimethylsiloxysilicate, trisiloxane, water, xanthan gum

Other information

• protect the product in this container from excessive heat and direct sun
• may stain or damage some fabrics, materials or surfaces